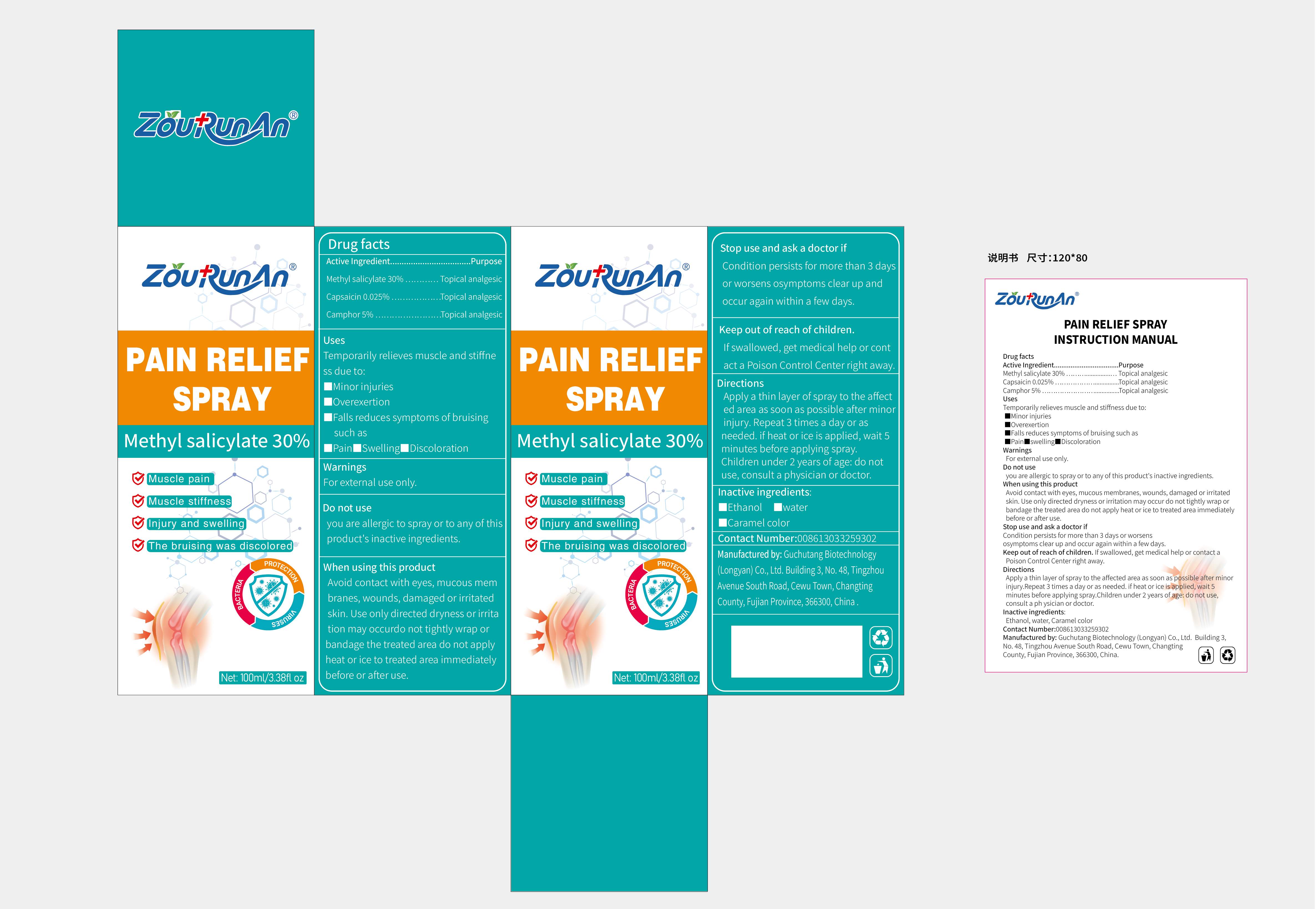 DRUG LABEL: zourunan PAIN RELIEF
NDC: 87083-006 | Form: SPRAY
Manufacturer: Guchutang Biotechnology (Longyan) Co., Ltd
Category: otc | Type: HUMAN OTC DRUG LABEL
Date: 20251022

ACTIVE INGREDIENTS: CAMPHOR (NATURAL) 5 g/100 mL; CAPSAICIN 0.025 g/100 mL; METHYL SALICYLATE 30 g/100 mL
INACTIVE INGREDIENTS: WATER; ALCOHOL; CARAMEL

87083-006

Active Ingredient

Methyl salicylate 30%
Capsaicin 0.025%
Camphor 5%

Purpose

Topical analgesic

Use

Temporarily relieves muscle and stiffness due to:
■minor injuries
■overexertion
■falls reduces symptoms of bruising such as
■pain■swelling■discoloration

Warnings

For external use only.

Do not use

you are allergic to spray or to any of this product's inactive ingredients.

When Using

Avoid contact with eyes, mucous mem branes, wounds, damaged or irritated skin. Use only directed dryness or irritation may occurdo not tightly wrap or bandage the treated area do not apply heat or ice to treated area immediately before or after use.

Stop Use

Condition persists for more than 3 days or worsens osymptoms clear up and occur again within a few days.

Ask Doctor

Condition persists for more than 3 days or worsens osymptoms clear up and occur again within a few days.

Keep Out Of Reach Of Children

If swallowed, get medical help or contact a Poison Control Center right away.

Directions

Apply a thin layer of spray to the affected area as soon as possible after minor injury.Repeat 3 times a day or as needed. if heat or ice is applied, wait 5 minutes before applying spray.Children under 2 years of age: do not use, consult a physician or doctor.

Inactive ingredients

Ethanol, water, Caramel color